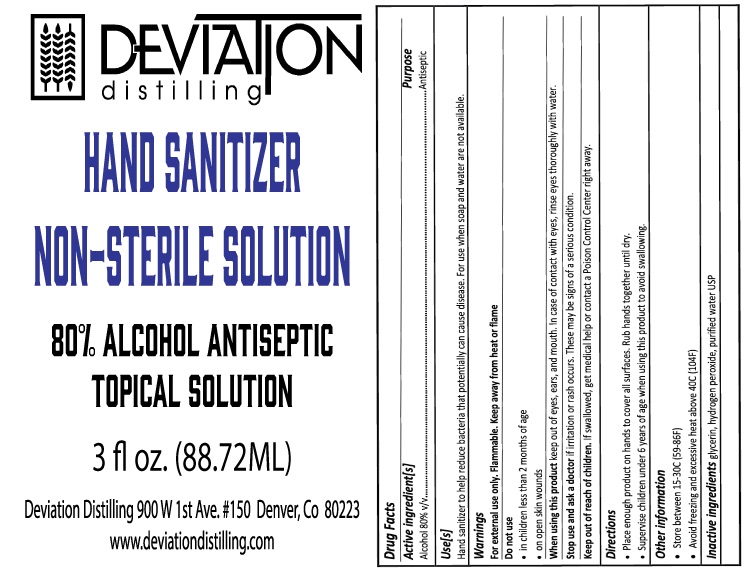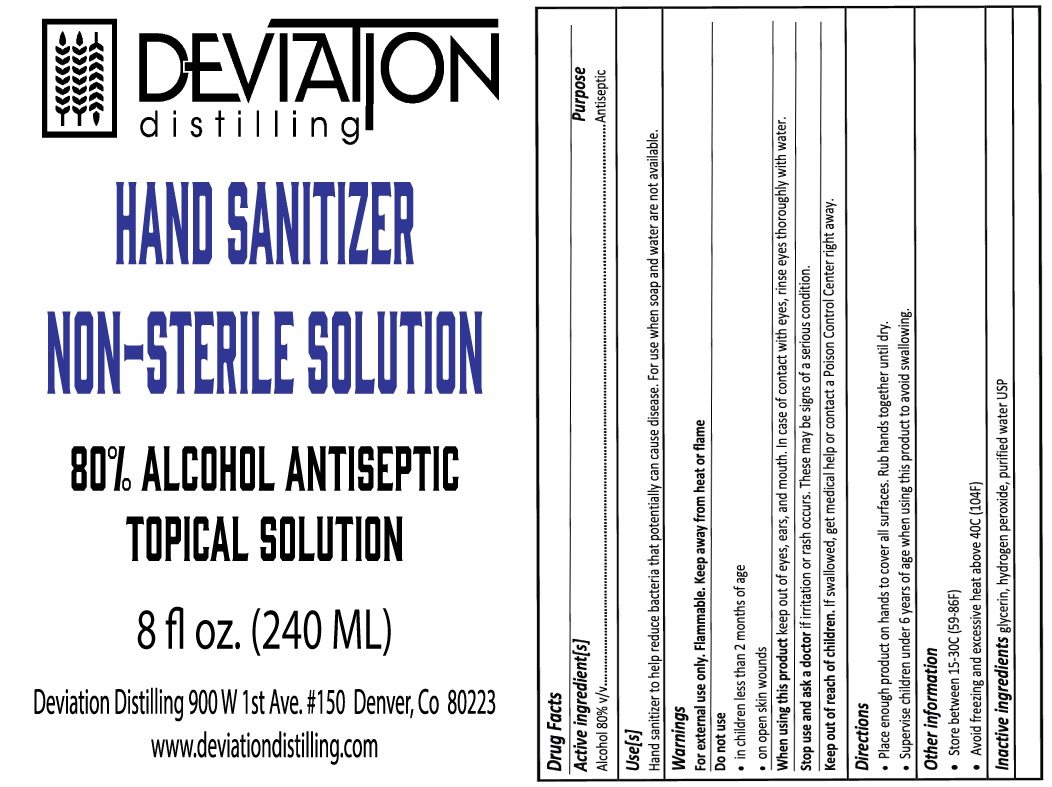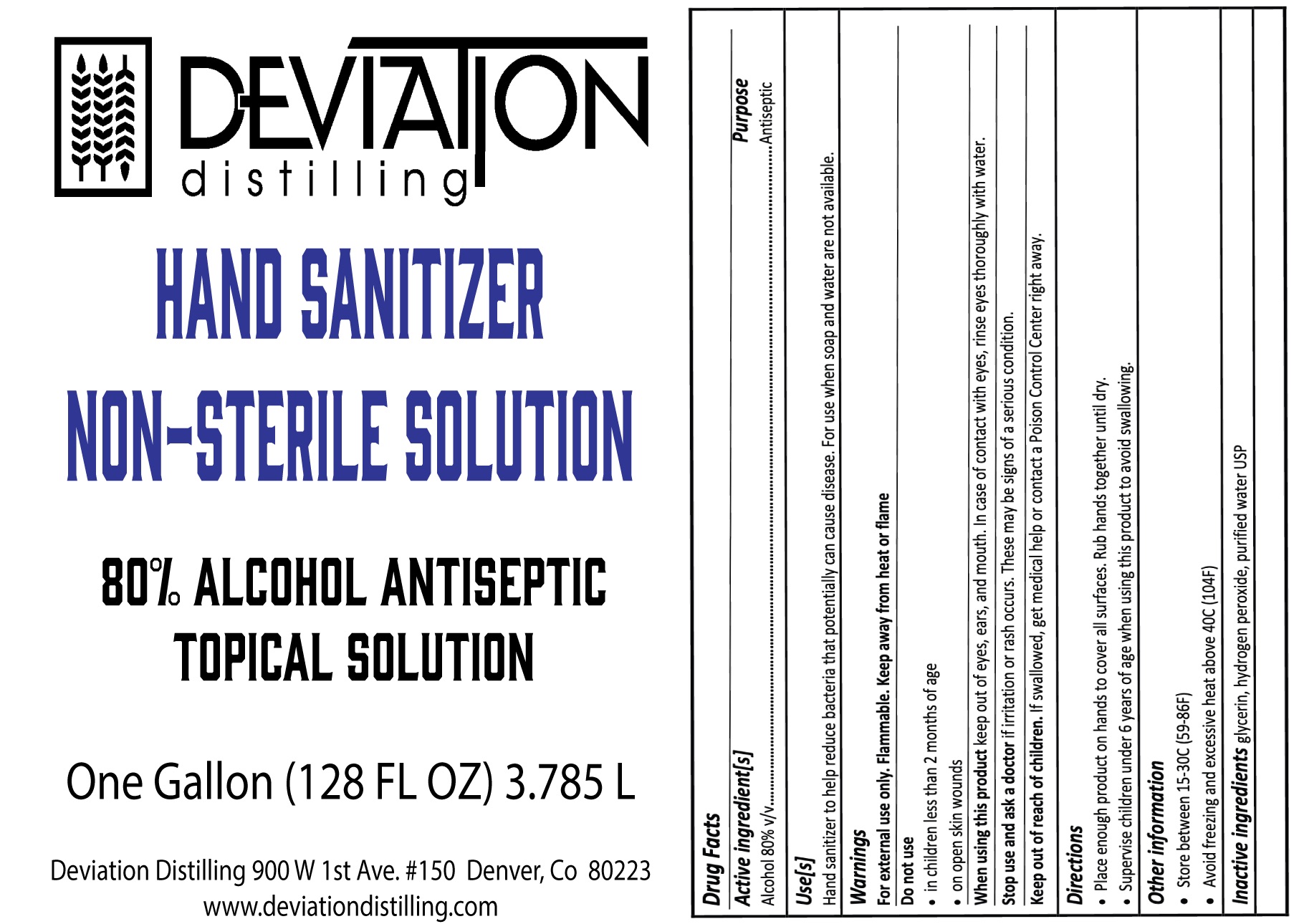 DRUG LABEL: Hand Sanitizer
NDC: 74105-900 | Form: LIQUID
Manufacturer: Deviation Distilling LLC
Category: otc | Type: HUMAN OTC DRUG LABEL
Date: 20200325

ACTIVE INGREDIENTS: ALCOHOL 80 mL/80 mL
INACTIVE INGREDIENTS: HYDROGEN PEROXIDE 0.125 mL/80 mL; GLYCERIN 1.45 mL/80 mL; WATER

ACTIVE INGREDIENT

ALCOHOL 80% V/V. PURPOSE: ANTISEPTIC

PURPOSE

ANTISEPTIC

DOSAGE AND ADMINISTRATION

Directions: Place enough product on hands to cover all surfaces. Rub hands together until dry.

WARNINGS

Warnings: For external use only. Flammable. Kepp away from heat or flame.

Inactive Ingredients: glycerin, hydrogen peroxide, purified water USP

INDICATIONS AND USAGE

Use(s): Hand santitizer to help reduce bacteria that potentially can cause disease. For use when soap and water are not available.

Keep out of reach of children: If swallowed, get medical help or contact a Poison Control Center right away.

PACKAGE LABEL

3785mL 74105-900-01

Hand Sanitizer Gallon.jpg

PACKAGE LABEL

236.59 mL 74105-900-08

PACKAGE LABEL

SIZE: 88.72 mL

NDC: 74105-900-03

IMAGE: 3oz bottle label.jpg